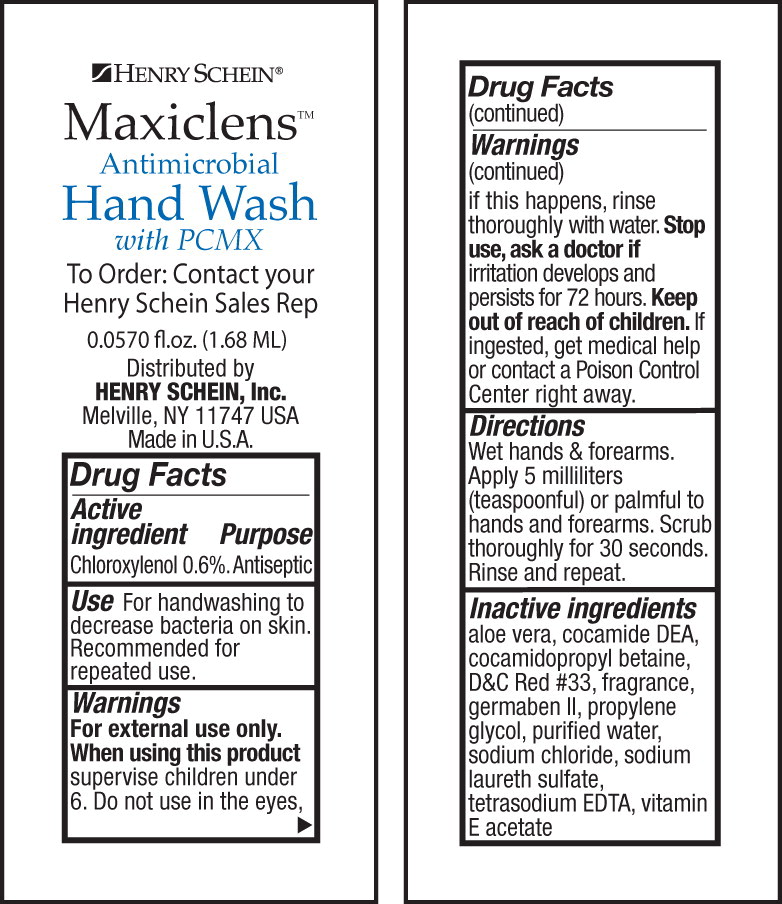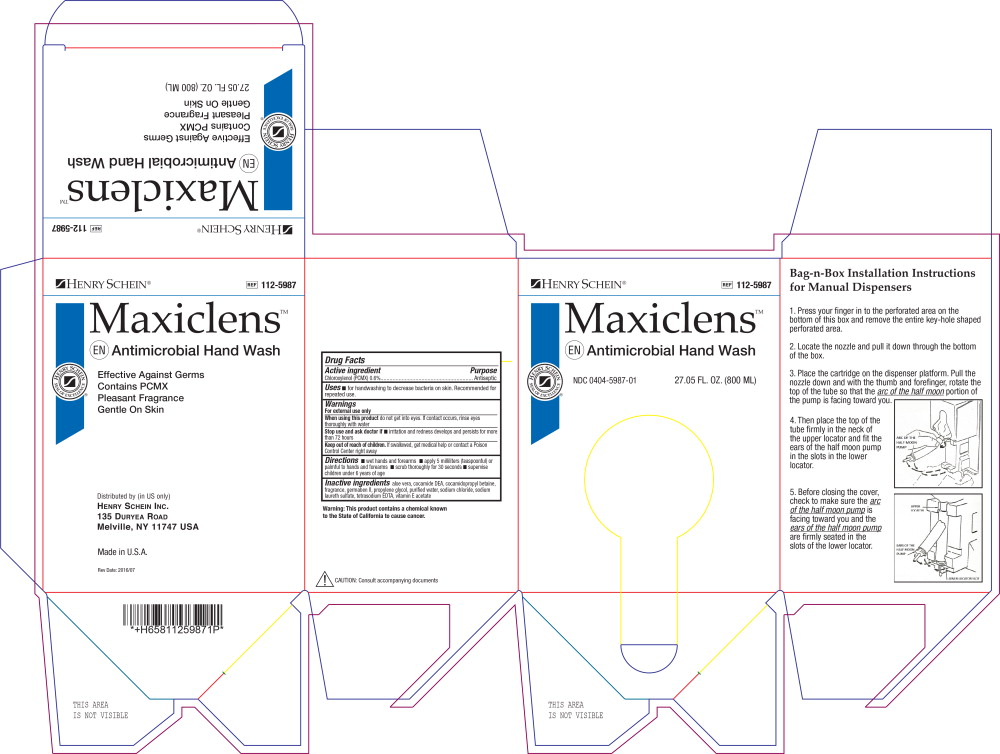 DRUG LABEL: Antimicrobial Hand Wash
NDC: 0404-5987 | Form: SOAP
Manufacturer: Henry Schein, Inc.
Category: otc | Type: HUMAN OTC DRUG LABEL
Date: 20160729

ACTIVE INGREDIENTS: chloroxylenol 6.0 mg/1000 mL
INACTIVE INGREDIENTS: aloe vera leaf; coco diethanolamide; cocamidopropyl betaine; diazolidinyl urea; propylene glycol; water; sodium chloride; sodium laureth sulfate; edetate sodium; alpha-tocopherol acetate; propylparaben; methylparaben

Drug Facts

Active Ingredient

Chloroxylenol (PCMX) 0.6%

Purpose

Antiseptic

Uses

- for handwashing to decrease bacteria on skin. Recommended for repeated use.

Warnings

For external use only.

When using this product do not get into eyes. If contact occurs, rinse eyes thoroughly with water

Stop use and ask doctor if

- irritation and redness develops and persists for more than 72 hours

Keep out of reach of children. If swallowed, get medical help or contact a Poison Control Center right away

Directions

- wet hands and forearms
- apply 5 milliliters (teaspoonful) or palmful to hands and forearms
- scrub thoroughly for 30 seconds
- supervise children under 6 years of age

Inactive Ingredients

aloe vera, cocamide DEA, cocamidopropyl betaine, D&C Red #33, fragrance, germaben II, propylene glycol, purified water, sodium chloride, sodium laureth sulfate, tetrasodium EDTA, vitamin E acetate

Distributed by HENRY SCHEIN, INC. Melville, NY 11747 USA

Made in U.S.A.

PRINCIPAL DISPLAY PANEL – 800 mL Box

Henry Schein

112-5987

Maxiclens

Antimicrobial Hand Wash

NDC 0404-5987-01

27.05 FL. OZ. (800 ML)

PRINCIPAL DISPLAY PANEL – 1.68 mL Packet

Henry Schein

Maxiclens

Antimicrobial

Hand Wash

With PCMX

To Order: Contact your
Henry Schein Sales Rep

0.0570 fl.oz. (1.68 ML)

Distributed by

HENRY SCHEIN, Inc.

Melville, NY 11747 USA

Made in U.S.A.